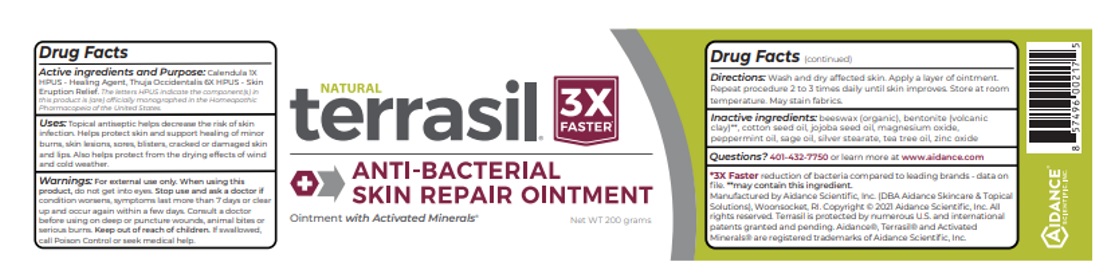 DRUG LABEL: Terrasil Antibacterial Skin Repair 200g
NDC: 24909-206 | Form: OINTMENT
Manufacturer: Aidance Skincare & Topical Solutions, LLC
Category: homeopathic | Type: HUMAN OTC DRUG LABEL
Date: 20240524

ACTIVE INGREDIENTS: THUJA OCCIDENTALIS WHOLE 6 [hp_X]/1 g; CALENDULA OFFICINALIS FLOWER 1 [hp_X]/1 g
INACTIVE INGREDIENTS: YELLOW WAX; BENTONITE; JOJOBA OIL; MAGNESIUM OXIDE; PEPPERMINT OIL; SAGE OIL; TEA TREE OIL; ZINC OXIDE; SILVER OXIDE; COTTONSEED OIL; STEARIC ACID

24909-206 terrasil Skin Repair Ointment

Active Ingredient and purpose

Calendula 1X HPUS - Healing Agent,
Thuja Occidentalis 6X HPUS - Skin Eruption Relief

The letters HPUS indicate the component(s) in this product (are) officially monographed in the Homeopathic Pharmacopeia of the United States

Uses

Topical antiseptic helps decrease the risk of skin infection. Helps protect skin and support healing of minor burns, skin lesions, sores, blisters, cracked or damaged skin and lips. Also helps protect from the drying effects of wind and cold weather.

Warnings

For external use only.
When using this product, do not get into eyes. Stop use and ask a doctor if condition worsens, symptoms last more than 7 days or clear up and occur again within a few days. Consult a doctor before using on a deep or puncture wounds, animal bites, or serious burns. Keep out of reach of children.If swallowed, call Poison Control or seek medical help.

Directions

Wash and dry affected skin. Apply a layer of ointment. Repeat procedure 2 to 3 times daily until skin improves. Store at room temperture. May stain fabrics.

Inactive Ingredients

beeswax(organic) bentonite (volcanic clay), jojoba seed oil, magnesium oxide, peppermint oil, sage oil, silver stearate, tea tree oil, zinc oxide, Cottonseed Oil, Stearic Acid

Questions?

401-432-7750 or www.aidance.com